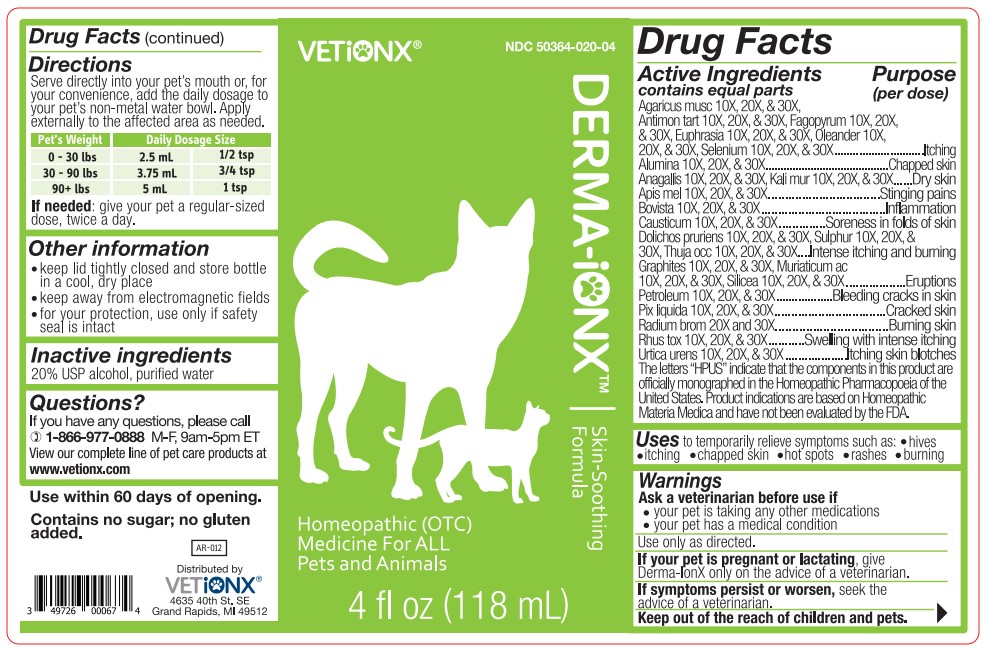 DRUG LABEL: Derma-iONX
NDC: 50364-020 | Form: LIQUID
Manufacturer: Ionx Holdings d/b/a VETiONX
Category: homeopathic | Type: OTC ANIMAL DRUG LABEL
Date: 20180601

ACTIVE INGREDIENTS: AMANITA MUSCARIA FRUITING BODY 30 [hp_X]/118 mL; ANTIMONY POTASSIUM TARTRATE 30 [hp_X]/118 mL; FAGOPYRUM ESCULENTUM 30 [hp_X]/118 mL; NERIUM OLEANDER LEAF 30 [hp_X]/118 mL; SELENIUM 30 [hp_X]/118 mL; ALUMINUM OXIDE 30 [hp_X]/118 mL; ANAGALLIS ARVENSIS 30 [hp_X]/118 mL; POTASSIUM CHLORIDE 30 [hp_X]/118 mL; APIS MELLIFERA 30 [hp_X]/118 mL; LYCOPERDON UTRIFORME FRUITING BODY 30 [hp_X]/118 mL; CAUSTICUM 30 [hp_X]/118 mL; MUCUNA PRURIENS FRUIT TRICHOME 30 [hp_X]/118 mL; SULFUR 30 [hp_X]/118 mL; GRAPHITE 30 [hp_X]/118 mL; HYDROCHLORIC ACID 30 [hp_X]/118 mL; KEROSENE 30 [hp_X]/118 mL; PINE TAR 30 [hp_X]/118 mL; RADIUM BROMIDE 30 [hp_X]/118 mL; TOXICODENDRON PUBESCENS LEAF 30 [hp_X]/118 mL; URTICA URENS 30 [hp_X]/118 mL; EUPHRASIA STRICTA 30 [hp_X]/118 mL; THUJA OCCIDENTALIS LEAFY TWIG 30 [hp_X]/118 mL; SILICON DIOXIDE 30 [hp_X]/118 mL
INACTIVE INGREDIENTS: WATER; ALCOHOL

Drug Facts

Active Ingredients

Agaricus musc 10X, 20X & 30X,

Antimon tart 10X, 20X & 30X,, Fagopyrum 10X, 20X & 30X,,

Euphrasia 10X, 20X & 30X, Oleander 10X, 20X & 30X,

Selenium 10X, 20X & 30X,
Alumina 10X, 20X & 30X,
Anagallis 10X, 20X & 30X, Kali Mur 10X, 20X & 30X
Apis mel 10X, 20X & 30X
Bovista 10X, 20X & 30X
Causticum 10X, 20X & 30X
Dolichos pruriens 10X, 20X & 30X, Sulphur 10X, 20X & 30X
Thuja occ 10X, 20X & 30X
Graphites, Muriaticum ac 10X, 20X & 30X,

Silicea 10X, 20X & 30X
Petroleum 10X, 20X & 30X
Pix liquida 10X, 20X & 30X
Radium brom 10X, 20X & 30X
Rhus tox 10X, 20X & 30X
Urtica urens 10X, 20X & 30X
The letters “HPUS” indicate that the components in this product are officially monographed in the Homeopathic Pharmacopoeia of the United States. Product indications are based on Homeopathic Materia Medica and have not been evaluated by the FDA.

Purpose (Per Dose)

Agaricus musc 10X, 20X & 30X, Antimon tart 10X, 20X & 30X, Fagopyrum 10X, 20X & 30X, Euphrasia 10X, 20X & 30X, Oleander 10X, 20X & 30X, Selenium 10X, 20X & 30X............................................................Itching

Alumina 10X, 20X & 30X..................................................................Chapped Skin
Anagallis 10X, 20X & 30X, Kali Mur 10X, 20X & 30X.............................Dry Skin
Apis mel 10X, 20X & 30X................................................................Stinging Pains

Bovista 10X, 20X & 30X....................................................................Inflammation
Causticum 10X, 20X & 30X...............................................................Soreness in folds of skin
Dolichos pruriens 10X, 20X & 30X, Sulphur 10X, 20X & 30X, Thuja occ 10X, 20X & 30X .................Intense itching and burning
Graphites, Muriaticum ac 10X, 20X & 30X, Silicea 10X, 20X & 30X.............................Eruptions

Petroleum 10X, 20X & 30X.............................................................Bleeding cracks in skin
Pix liquida 10X, 20X & 30X..........................................................Cracked skin
Radium brom 10X, 20X & 30X.....................................................Burning skin
Rhus tox 10X, 20X & 30X..........................................................Swelling with intense itching
Urtica urens 10X, 20X & 30X....................................................Itching skin blotches

The letters “HPUS” indicate that the components in this product are officially monographed in the Homeopathic Pharmacopoeia of the United States. Product indications are based on Homeopathic Materia Medica and have not been evaluated by the FDA.

Uses

to temporarily relieve symptoms such as:

- Hives
- Itching
- chapped skin
- hot spots
- rashes
- burning

Warnings

Ask a veterinarian before use if

- your pet is taking any other medications
- your pet has a medical condition

Use only as directed.

PREGNANCY OR BREAST FEEDING

If your pet is pregnant or lactating, give Derma-IonX only on the advice of a veterinarian.

ASK DOCTOR

If symptoms persist or worsen, seek the advice of a veterinarian.

KEEP OUT OF REACH OF CHILDREN

Keep out of the reach of children and pets.

Directions

Serve directly into your pet's mouth or, for your convenience, add the daily dosage to your pet's non-metal water bowl. Apply externally to the affected area as needed.

Pet's Weight Daily Dosage Size

0-30 lbs 2.5 mL 1/2 tsp

30-90 lbs 3.75 mL 3/4 tsp

90+ lbs 5 mL 1 tsp

If needed: give your pet a regular-sized dose, twice a day.

Other information

- keep lid tightly closed and store bottle in a cool, dry place
- keep away from electromagnetic fields
- for your protection, use only if safety seal is intact

Inactive ingredients

20% USP Alcohol, purified water

Questions?

If you have any questions, please call 1-866-977-0888 M-F, 9am-5pm ET. View our complete line of pet care products at www.vetionx.com

DESCRIPTION

Use within 60 days of opening.

Contains no sugar; no gluten added.

Distributed by

VETiONX

4635 40th St. SE

Grand Rapids, MI 49512

PACKAGE LABEL

50364-020-04

DERMA-iONX
Skin-Soothing Formula

Homeopathic (OTC) Medicine

For ALL Pets and Animals

4 fl oz (118 mL)